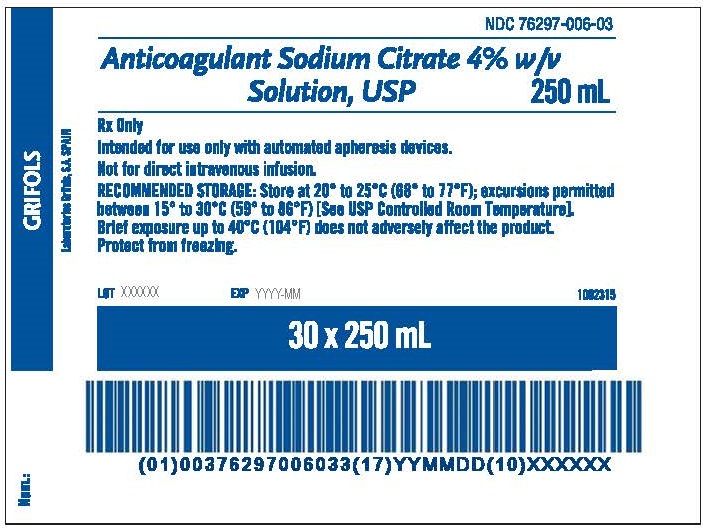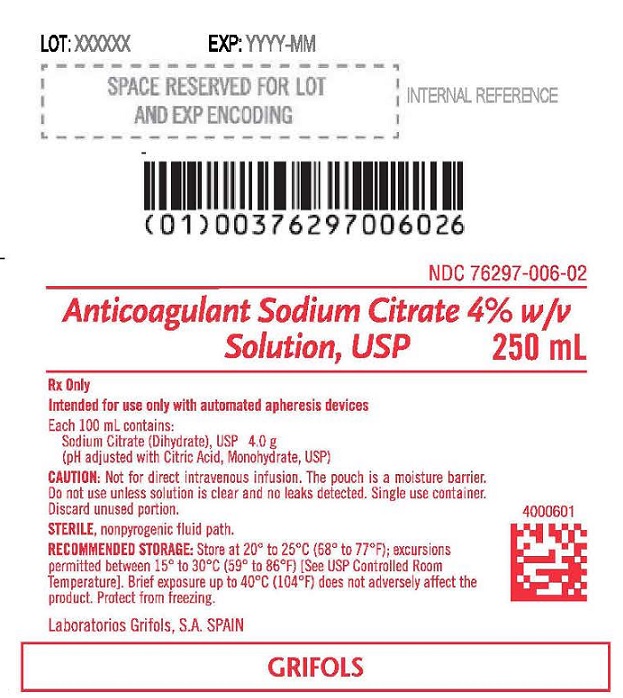 DRUG LABEL: Anticoagulant Sodium Citrate
NDC: 76297-006 | Form: SOLUTION
Manufacturer: LABORATORIOS GRIFOLS SA
Category: prescription | Type: HUMAN PRESCRIPTION DRUG LABEL
Date: 20240405

ACTIVE INGREDIENTS: Trisodium Citrate Dihydrate 40 mg/1 mL
INACTIVE INGREDIENTS: Water; Citric Acid Monohydrate

Anticoagulant Sodium Citrate

ANTICOAGULANT SODIUM CITRATE 4% w/v SOLUTION USP

Rx only 250 mL
Intended for use only with automated apheresis devices.
Each 100 mL contains:
Sodium Citrate (Dihydrate), USP 4.0 g
(pH adjusted with Citric Acid, Monohydrate, USP)

CAUTION

Not for direct intravenous infusion. The pouch is a moisture barrier. Do not use unless solution is clear and no leaks detected. Single use container. Discard unused portion.

STERILE, nonpyrogenic fluid path.

RECOMMENDED STORAGE:

Store at 20°C to 25°C (68°F to 77°F); excursions permitted between 15°C to 30°C (59°F to 86°F) [See USP Controlled Room Temperature]. Brief exposure up to 40°C (104°F) does not adversely affect the product. Protect from freezing.

Laboratorios Grifols, S. A.
SPAIN
Revision: 10/2019

PACKAGE LABEL.PRINCIPAL DISPLAY PANEL

NDC 76297-006-03
Anticoagulant Sodium Citrate 4% w/v
Solution, USP 250 mL
Rx Only
Intended for use only with automated apheresis devices.
Not for direct intravenous infusion.
RECOMMENDED STORAGE: Store at 20° to 25°C (68° to 77°F); excursions permitted
between 15° to 30°C (59° to 86°F) [See USP Controlled Room Temperature].
Brief exposure up to 40°C (104°F) does not adversely affect the product.
Protect from freezing.
LOT XXXXXX EXP YYYY-MM
30 x 250 mL
Num.:
GRIFOLS
Laboratorios Grifols, S. A. SPAIN

LOT: XXXXXX EXP: YYYY-MM
NDC 76297-006-02
Anticoagulant Sodium Citrate 4% w/v
Solution, USP 250 mL
Rx Only
Intended for use only with automated apheresis devices
Each 100 mL contains:
Sodium Citrate (Dihydrate), USP 4.0 g
(pH adjusted with Citric Acid, Monohydrate, USP)
Caution: Not for direct intravenous infusion. The pouch is a moisture barrier.
Do not use unless solution is clear and no leaks detected. Single use container.
Discard unused portion.
STERILE, nonpyrogenic fluid path.
RECOMMENDED STORAGE: Store at 20° to 25°C (68° to 77°F); excursions
permitted between 15° to 30°C (59° to 86°F) [See USP Controlled Room
Temperature]. Brief exposure up to 40°C (104°F) does not adversely affect the
product. Protect from freezing.
Laboratorios Grifols, S. A. SPAIN
GRIFOLS